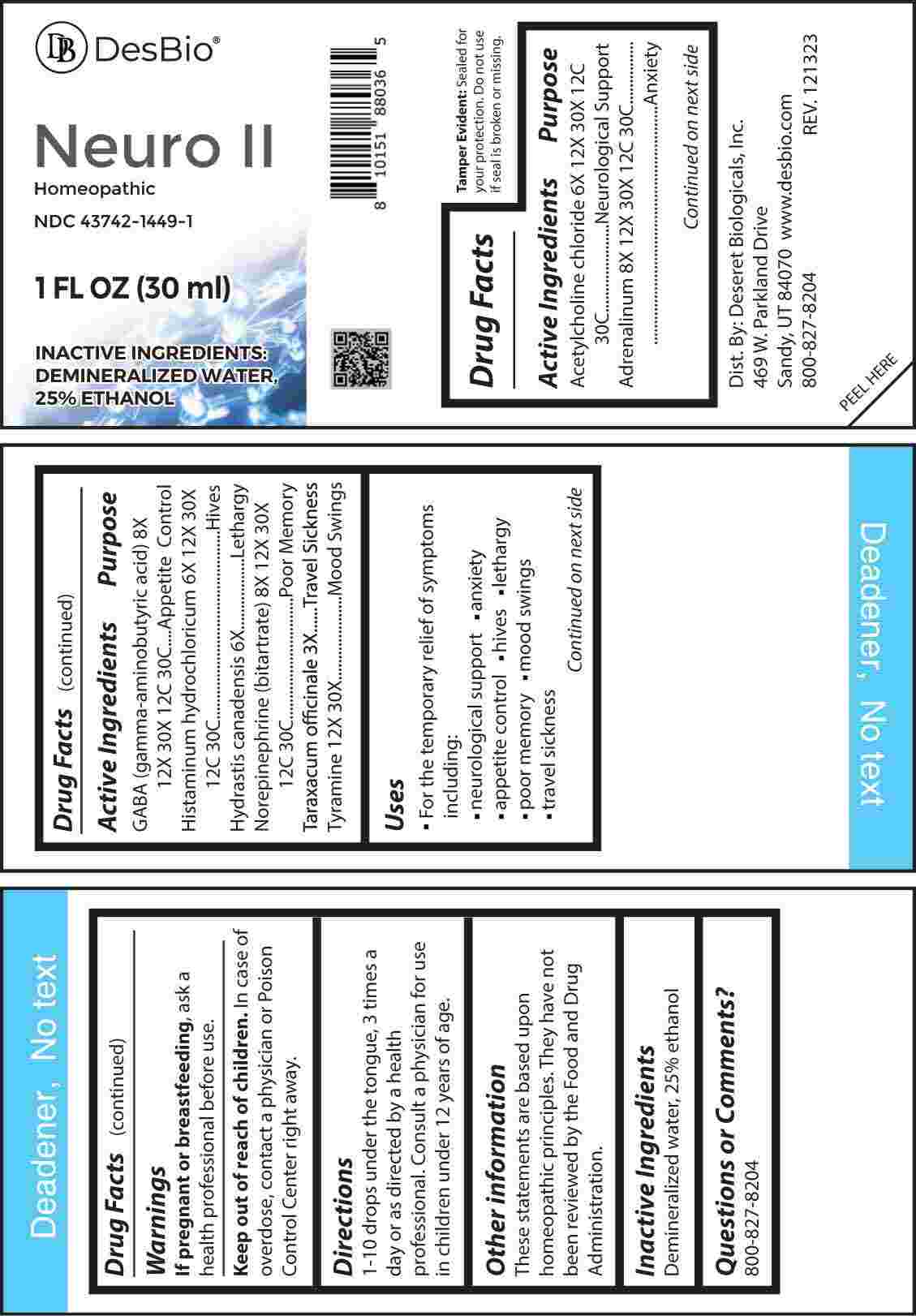 DRUG LABEL: Neuro
NDC: 43742-1449 | Form: LIQUID
Manufacturer: Deseret Biologicals, Inc.
Category: homeopathic | Type: HUMAN OTC DRUG LABEL
Date: 20240401

ACTIVE INGREDIENTS: TARAXACUM OFFICINALE 3 [hp_X]/1 mL; GOLDENSEAL 6 [hp_X]/1 mL; ACETYLCHOLINE CHLORIDE 6 [hp_X]/1 mL; HISTAMINE DIHYDROCHLORIDE 6 [hp_X]/1 mL; EPINEPHRINE 8 [hp_X]/1 mL; .GAMMA.-AMINOBUTYRIC ACID 8 [hp_X]/1 mL; NOREPINEPHRINE BITARTRATE 8 [hp_X]/1 mL; TYRAMINE 12 [hp_X]/1 mL
INACTIVE INGREDIENTS: WATER; ALCOHOL

DRUG FACTS:

ACTIVE INGREDIENTS:

Acetylcholine Chloride 6X, 12X, 30X, 12C, 30C, Adrenalinum 8X, 12X, 30X, 12C, 30C, GABA (Gamma-Aminobutyric Acid) 8X, 12X, 30X, 12C, 30C, Histaminum Hydrochloricum 6X, 12X, 30X, 12C, 30C, Hydrastis Canadensis 6X, Norepinephrine (Bitartrate) 8X, 12X, 30X, 12C, 30C, Taraxacum Officinale 3X, Tyramine 12X, 30X.

PURPOSE:

Acetylcholine Chloride – Neurological Support, Adrenalinum - Anxiety, GABA (Gamma-Aminobutyric Acid) – Appetite Control, Histaminum Hydrochloricum - Hives, Hydrastis Canadensis - Lethargy, Norepinephrine (Bitartrate) – Poor Memory, Taraxacum Officinale – Travel Sickness, Tyramine – Mood Swings

USES:

• For the temporary relief from symptoms including:

• neurological support • anxiety • appetite control • hives

• lethargy • poor memory • mood swings • travel sickness

These statements are based upon homeopathic principles. They have not been reviewed by the Food and Drug Administration.

WARNINGS:

If pregnant or breast-feeding, ask a health professional before use.

Keep out of reach of children. In case of overdose, contact a physician or Poison Control Center right away.

Tamper Evident: Sealed for your protection. Do not use if seal is broken or missing.

KEEP OUT OF REACH OF CHILDREN:

In case of overdose, contact a physician or Poison Control Center right away.

DIRECTIONS:

1-10 drops under the tongue, 3 times a day or as directed by a health professional. Consult a physician for use in children under 12 years of age.

INACTIVE INGREDIENTS:

Demineralized water, 25% ethanol

QUESTIONS:

Dist. By: Deseret Biologicals, Inc.
469 W. Parkland Drive
Sandy, UT 84070

www.desbio.com

800-827-8204

PACKAGE LABEL DISPLAY:

Des Bio

Neuro II

Homeopathic
NDC 43742-1449-1
1 FL OZ (30 ml)